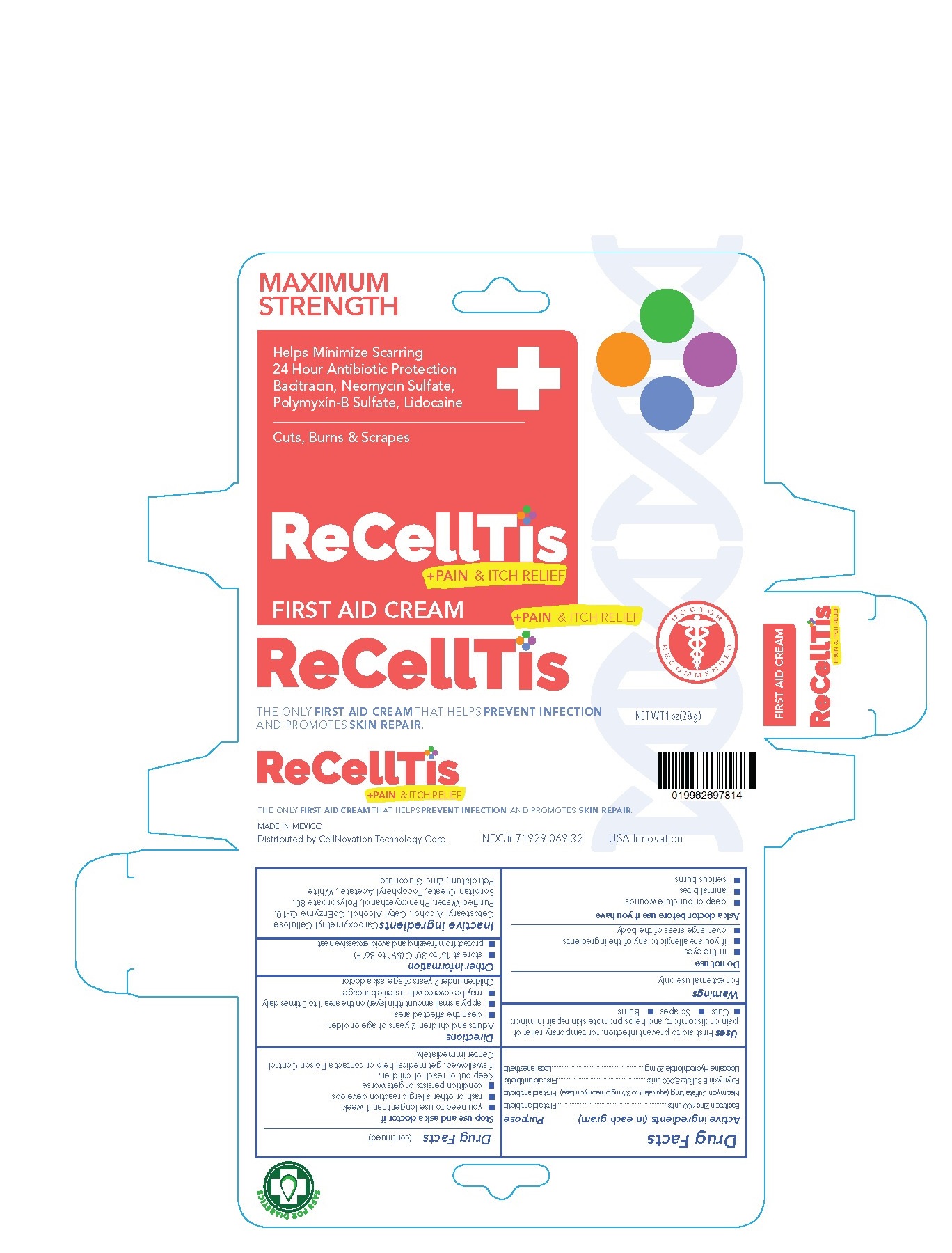 DRUG LABEL: ReCellTis
NDC: 71929-069 | Form: CREAM
Manufacturer: CellNovation Technology Corporation
Category: otc | Type: HUMAN OTC DRUG LABEL
Date: 20180321

ACTIVE INGREDIENTS: BACITRACIN ZINC 400 [USP'U]/1 g; NEOMYCIN SULFATE 3.5 mg/1 g; POLYMYXIN B SULFATE 5000 [USP'U]/1 g; LIDOCAINE 20 mg/1 g
INACTIVE INGREDIENTS: COENZYME Q10, (2Z)-; POLYSORBATE 80; PETROLATUM; CETOSTEARYL ALCOHOL; CARBOXYMETHYLCELLULOSE; WATER; PHENOXYETHANOL; PEG-6 SORBITAN OLEATE; ALPHA-TOCOPHEROL ACETATE; ZINC GLUCONATE; CETYL ALCOHOL

ReCellTis

ReCellTis +Pain & Itch Relief First Aid Cream

Drug Facts

Active Ingredients (in each gram)

Bacitracin Zinc 400 units

Neomycin Sulfate 5mg (equivalent to 3.5 mg of neomycin base)

Polymyxin B Sulfate 5,000 units

Lidocaine Hydrochloride 20 mg

Purpose

First aid antibiotic

First aid antibiotic

First aid antibiotic

Local anesthetic

Uses

First aid to prevent infection, for temporary relief of pain or discomfort, and helps promote skin repair in minor:

- Cuts
- Scrapes
- Burns

Warnings

For external use only

Do not use

- in the eyes
- if you are allergic to any of the ingredients
- over large areas of the body

Ask a doctor before use if you have

- deep or puncture wounds
- animal bites
- serious burns

Stop use and ask a doctor if

- you need to use longer than 1 week
- rash or other allergic reaction develops
- condition persists or gets worse

Keep out of reach of children.

If swallowed, get medical help or contact a Poison Control Center immediately.

Directions

Adults and children 2 years of age or older:

- clean the affected area
- apply a small amount (thin layer) on the area 1 to 3 times daily
- may be covered with sterile bandage

Children under 2 years of age: ask a doctor

Other Information

- store at 15° to 30°C (59° to 86°F)
- protect from freezing and avoid excessive heat

Inactive ingredients

Carboxymethyl Cellulose, Cetostearyl Alcohol, Cetyl Alcohol, CoEnzyme Q-10, Purified Water, Phenoxyethanol, Polysorbate 80, Sorbitan Oleate, Tocopheryl Acetate , White Petrolatum, Zinc Gluconate.